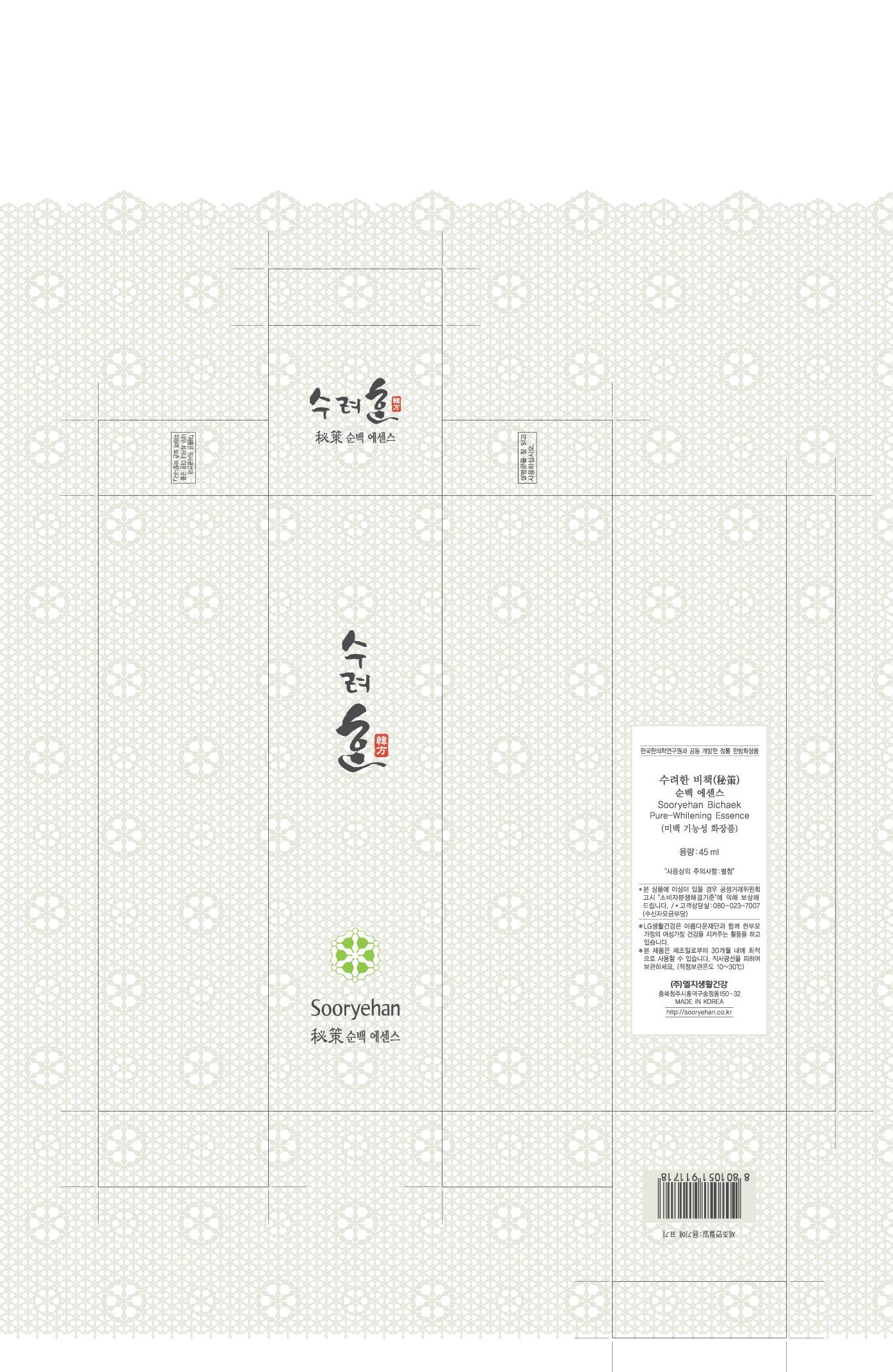 DRUG LABEL: Sooryehan Pure-Whitening Essence
NDC: 53208-442 | Form: CREAM
Manufacturer: LG Household and Healthcare, Inc.
Category: otc | Type: HUMAN OTC DRUG LABEL
Date: 20100514

ACTIVE INGREDIENTS: POLYDATIN 0.22 1/100 mL
INACTIVE INGREDIENTS: WATER; GLYCERIN; DIPROPYLENE GLYCOL; DIMETHICONE; PANTHENOL; POLYOXYL 40 HYDROGENATED CASTOR OIL; METHYLPARABEN; TROLAMINE; ETHYLPARABEN; EDETATE TRISODIUM; FD&C YELLOW NO. 5; FD&C YELLOW NO. 6

DRUG FACTS

ACTIVE INGREDIENT

POLYDATIN 0.22mL/100mL

WARNINGS AND PRECAUTIONS

For external use only.

Keep out of reach of children. Is swallowed, get medical help or contact a Poison Control Center right away.

Stop use if a rash or irritation develops and lasts.

PACKAGE LABEL

Sooryehan